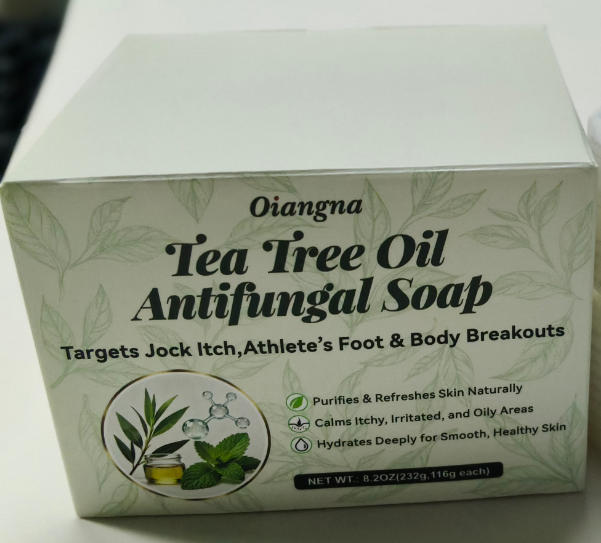 DRUG LABEL: Oiangna Tea Tree Oil Antifungal
NDC: 87204-285 | Form: SOAP
Manufacturer: Guangzhou Huixue Biotechnology Co., Ltd.
Category: otc | Type: HUMAN OTC DRUG LABEL
Date: 20251205

ACTIVE INGREDIENTS: CLOTRIMAZOLE 1 g/116 g
INACTIVE INGREDIENTS: BISABOLOL; STEARIC ACID; SORBITOL; OLIVE OIL; PALM OIL; SODIUM HYDROXIDE; ALLANTOIN; PHENOXYETHANOL; AQUA; TEA TREE OIL; ETHYLHEXYLGLYCERIN

ACTIVE INGREDIENT

Clotrimazole 1%

INACTIVE INGREDIENT

Tea Tree Oil, Aqua,Sorbitol,Palm Oil,Coconut Oil Extract, Elaeis Guineensis (palm) Fruit Oil, Coconut Oil Extract,Olive Oil,Propylene Glycol,Ethylhexylglycerin,Stearic Acid,Sorbitol,vitamin E,Allantoin,Ceramide,Sodium Hydroxide,Phenoxyethanol,Bisabolol,Zingiber Officinale (ginger) Root Extract,Witch Hazel Extract,Aloe Vera Extract,Calendula Extract

PURPOSE

Relieves and helps prevent recurrence of: -Athlete's foot (tinea pedis) - Jock itch (tinea cruris) -Ringworm (tinea corporis) -Helps reduce body odor, acne, itching, eczema, and irritatedd skincaused by fungi

INDICATIONS AND USAGE

Apply soap to wet skin and lather.

Massage gently into affected areas for 30 seconds.

Rinse thoroughly and dry compietely.

Use twice daily or as directed by a healthcare provider.

WARNINGS

For external use only Ask a doctor before use if you have a deep or serious fungal infection. Avoid contact with eyes. If contact occurs, rinse thoroughly with water. If irritation or redness develops, stop use and consult a physician. Keep out of reach of children.

KEEP OUT OF REACH OF CHILDREN

If swallowed, get medical help or contact a Poison Control Center right away.

WHEN USING

Apply soap to wet skin and lather.

Massage gently into affected areas for 30 seconds.
Rinse thoroughly and dry completely.
Use twice daily or as directed by a healthcare provider.

You do not know the reason .
You ae under 18 years of age, Do not use it on babies and children your Skin is red.
You use other medicines on the Skin.Ask a doctor before use if you hace heart disease.

STOP USE

Chest pain, rapid heart beat, faintness, or dizziness occurs sudden, unexplained weight gain occurs,your hands or feet swell.

DOSAGE AND ADMINISTRATION

Massage gently into affected areas for 30 seconds.

Use twice daily or as directed by a healthcare provider.